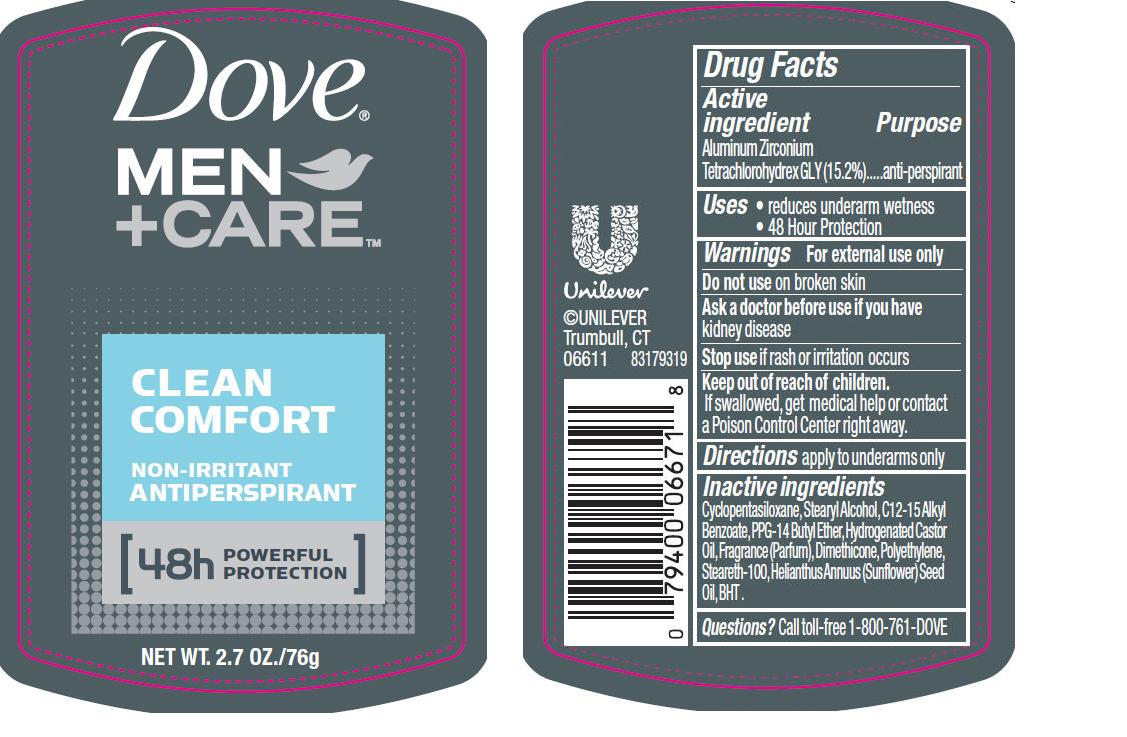 DRUG LABEL: Dove
NDC: 64942-1218 | Form: STICK
Manufacturer: Conopco Inc. d/b/a Unilever
Category: otc | Type: HUMAN OTC DRUG LABEL
Date: 20221205

ACTIVE INGREDIENTS: ALUMINUM ZIRCONIUM TETRACHLOROHYDREX GLY 15.2 g/100 g
INACTIVE INGREDIENTS: CYCLOMETHICONE 5; PPG-14 BUTYL ETHER; STEARYL ALCOHOL; HYDROGENATED CASTOR OIL; DIMETHICONE; BUTYLATED HYDROXYTOLUENE; STEARETH-100; SUNFLOWER OIL; ALKYL (C12-15) BENZOATE; HIGH DENSITY POLYETHYLENE

Dove Clean Comfort Antiperspirant deodorant

Active Ingredient

Aluminum Zirconium Tetrachlorohydrex GLY (15.2%)

Purpose

anti-perspirant

Uses

· reduces underarm wetness

· 48 hour protection

Warnings
For External Use Only

Do not use on broken skin

Ask a doctor before use if you have kidney disease

Stop use if rash or irritation occurs

Directions

· apply to underarms only

Keep out of reach of children. If swallowed, get medical help or contact a Poison Control Center right away

Questions?

Call toll-free 1-800-761-DOVE

Inactive ingredients

Ingredients: Cyclopentasiloxane, Stearyl Alcohol, C12-15 Alkyl Benzoate, PPG-14 Butyl Ether, Hydrogenated Castor Oil,
Fragrance (Parfum), Dimethicone, Polyethylene, Steareth-100, Helianthus Annuus (Sunflower) Seed Oil, BHT.